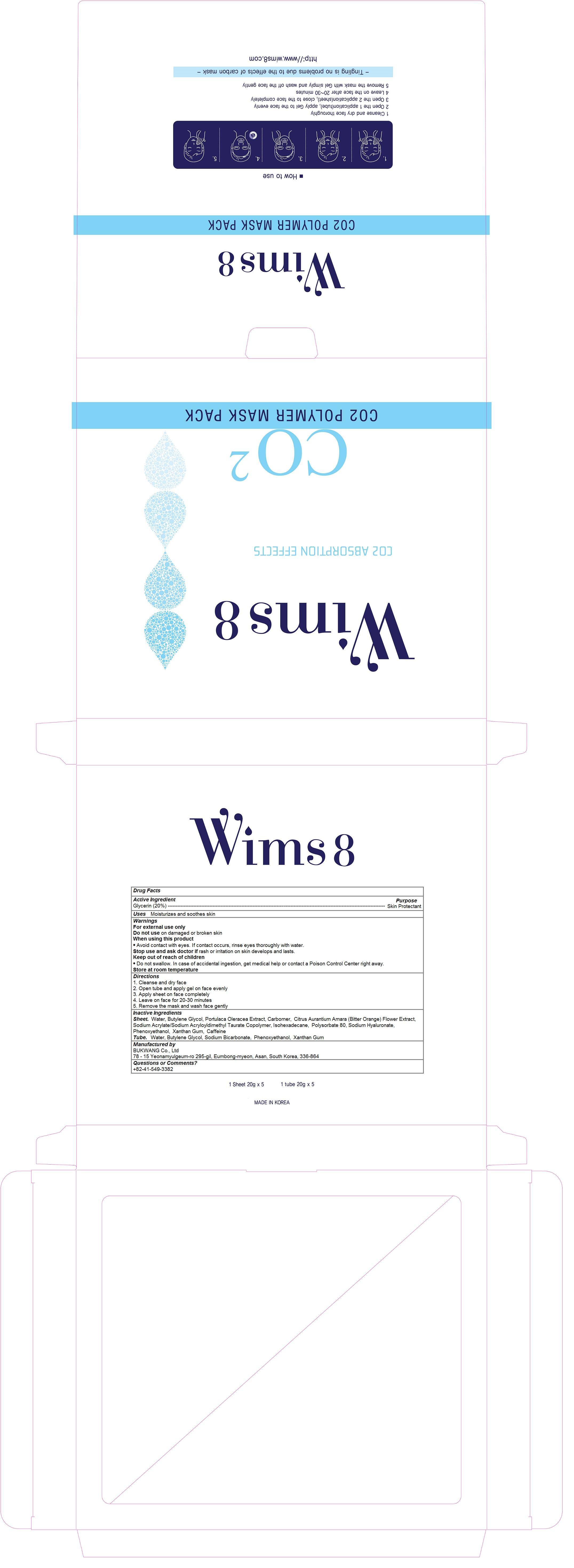 DRUG LABEL: Co2 Polymer Mask Pack
NDC: 69704-100 | Form: KIT | Route: TOPICAL
Manufacturer: BUKWANG Co.,Ltd
Category: otc | Type: HUMAN OTC DRUG LABEL
Date: 20150327

ACTIVE INGREDIENTS: GLYCERIN 0.1 1/20 g; GLYCERIN 0.1 1/20 g
INACTIVE INGREDIENTS: water; BUTYLENE GLYCOL; PORTULACA OLERACEA WHOLE; CARBOMER HOMOPOLYMER TYPE A (ALLYL PENTAERYTHRITOL CROSSLINKED); CITRUS AURANTIUM FLOWER; SODIUM ACRYLATE; ISOHEXADECANE; POLYSORBATE 80; HYALURONATE SODIUM; PHENOXYETHANOL; XANTHAN GUM; CAFFEINE; water; butylene glycol; SODIUM BICARBONATE; PHENOXYETHANOL; xanthan gum

Co2 Polymer Mask Pack